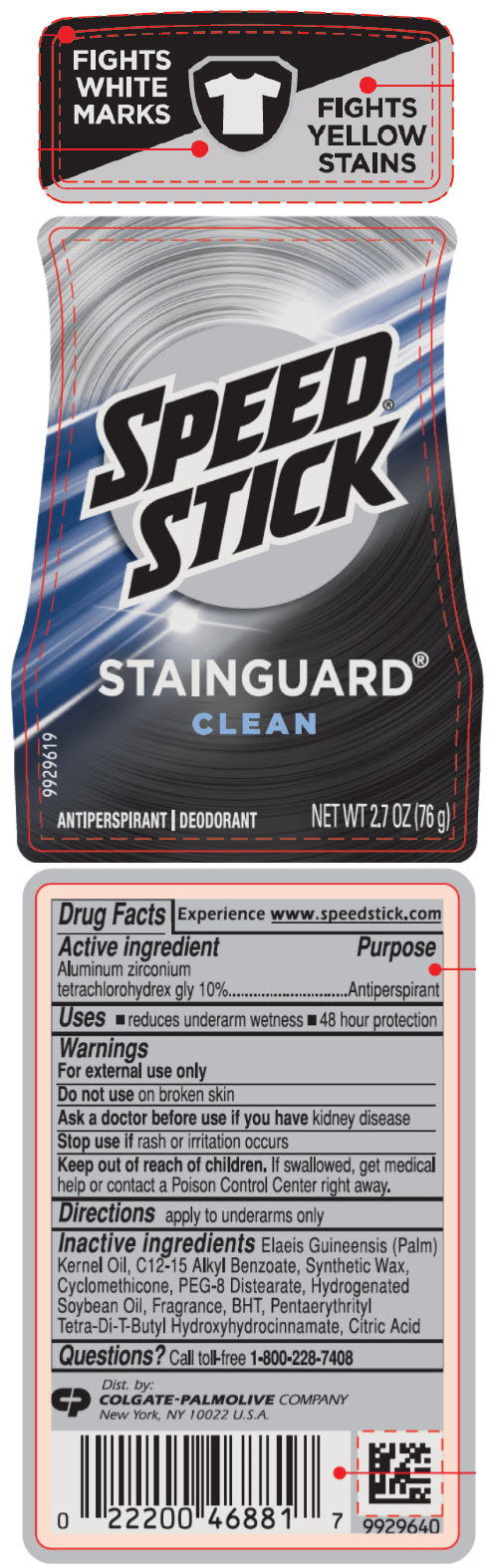 DRUG LABEL: Mens Speed Stick Stainguard Clean - antiperspirant/deodorant
NDC: 35000-666 | Form: STICK
Manufacturer: COLGATE PALMOLIVE COMPANY
Category: otc | Type: HUMAN OTC DRUG LABEL
Date: 20210525

ACTIVE INGREDIENTS: ALUMINUM ZIRCONIUM TETRACHLOROHYDREX GLY 100 mg/1 g
INACTIVE INGREDIENTS: PALM KERNEL OIL; ALKYL (C12-15) BENZOATE; CYCLOMETHICONE; PEG-8 DISTEARATE; HYDROGENATED SOYBEAN OIL; BUTYLATED HYDROXYTOLUENE; PENTAERYTHRITOL TETRAKIS(3-(3,5-DI-TERT-BUTYL-4-HYDROXYPHENYL)PROPIONATE); CITRIC ACID MONOHYDRATE

Mens Speed® Stick Stainguard® Clean - antiperspirant/deodorant (2.7 oz)

Drug Facts

Active ingredient

Aluminum zirconium tetrachlorohydrex gly 10%

Purpose

Antiperspirant

Uses

- reduces underarm wetness
- 48 hour protection

Warnings

For external use only

Do not use on broken skin

Ask a doctor before use if you have kidney disease

Stop use if rash or irritation occurs

Keep out of reach of children. If swallowed, get medical help or contact a Poison Control Center right away.

Directions

apply to underarms only

Inactive ingredients

Elaeis Guineensis (Palm) Kernel Oil, C12-15 Alkyl Benzoate, Synthetic Wax, Cyclomethicone, PEG-8 Distearate, Hydrogenated Soybean Oil, Fragrance, BHT, Pentaerythrityl Tetra-Di-T-Butyl Hydroxyhydrocinnamate, Citric Acid

Questions?

Call toll-free 1-800-228-7408

Dist. by:
COLGATE-PALMOLIVE COMPANY
New York, NY 10022 U.S.A.

PRINCIPAL DISPLAY PANEL - 76 g Container Label

FIGHTS
WHITE
MARKS

FIGHTS
YELLOW
STAINS

SPEED®
STICK

STAINGUARD®
CLEAN

9929619

ANTIPERSPIRANT | DEODORANT
NET WT 2.7 OZ (76 g)